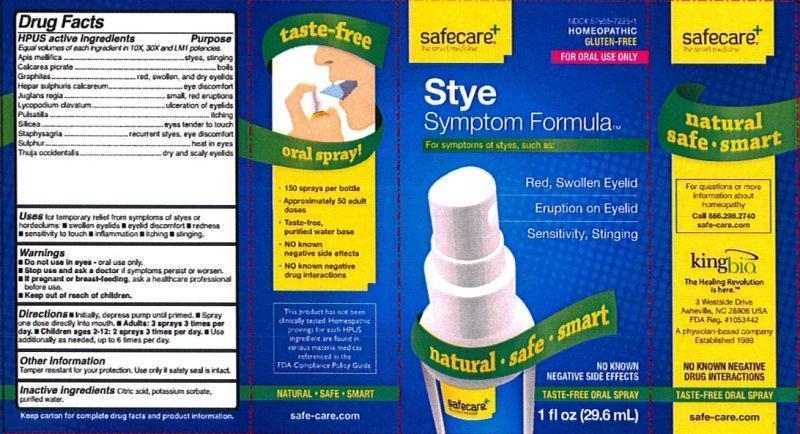 DRUG LABEL: Stye Symptom Formula
NDC: 57955-7225 | Form: LIQUID
Manufacturer: King Bio Inc.
Category: homeopathic | Type: HUMAN OTC DRUG LABEL
Date: 20140108

ACTIVE INGREDIENTS: APIS MELLIFERA 10 [hp_X]/29.6 mL; CALCIUM PICRATE 10 [hp_X]/29.6 mL; GRAPHITE 10 [hp_X]/29.6 mL; CALCIUM SULFIDE 10 [hp_X]/29.6 mL; JUGLANS REGIA WHOLE 10 [hp_X]/29.6 mL; LYCOPODIUM CLAVATUM SPORE 10 [hp_X]/29.6 mL; PULSATILLA VULGARIS 10 [hp_X]/29.6 mL; SILICON DIOXIDE 10 [hp_X]/29.6 mL; DELPHINIUM STAPHISAGRIA SEED 10 [hp_X]/29.6 mL; SULFUR 10 [hp_X]/29.6 mL; THUJA OCCIDENTALIS LEAFY TWIG 10 [hp_X]/29.6 mL
INACTIVE INGREDIENTS: CITRIC ACID MONOHYDRATE; POTASSIUM SORBATE; WATER

Stye Symptom Formula™

Drug Facts

____________________________________________________________________________________________________________

Equal volumes of each ingredient in 10X, 30X, and LM1 potencies.

HPUS active ingredients: Apis mellifica, Calcarea picrata, graphites, Hepar sulphuris calcareum, Juglans regia, Lycopodium clavatum, Pulsatilla, Silicea, Staphysagria, Sulphur, Thuja occidentalis.

INDICATIONS AND USAGE

Uses for temporary relief from symptoms of styes or hordeolums:

- swollen eyelids
- eyelid discomfort
- redness
- sensitivity to touch
- inflammation
- itching
- stinging

Warnings

- Do not use in eyes - oral use only
- Stop use and ask a doctor if symptoms persist or worsen.
- If pregnant or breast-feeding, ask a healthcare professional before use.

- Keep out of reach of children.

Directions:

- Initially, depress pump until primed.
- Spray one dose directly into mouth.
- Adults: 3 sprays 3 times per day.
- Children ages 2-12: 2 sprays 3 times per day.
- Use additionally as needed, up to 6 times per day.

Other Information

- Tamper resistant for your protection.
- Use only if safety seal is intact.

Inactive Ingredients: Citric acid, potassium sorbate, purified water.

Drug Facts

__________________________________________________________________________________________________________________

HPUS active ingredients Purpose

Equal volumes of each ingredient in 10X, 30X, and LM1 potencies.

Apis mellifica.............................................................................styes, stinging

Calcarea picrata.........................................................................boils

Graphites..................................................................................red, swollen, and dry eyelids

Hepar sulphuris calcareum..........................................................eye discomfort

Juglans regia.............................................................................small, red eruptions

Lycopodium clavatum.................................................................ulceration of eyelids

Pulsatilla...................................................................................itching

Silicea......................................................................................eyes tender to touch

Staphysagria.............................................................................recurrent styes, eye discomfort

Sulphur....................................................................................heat in eyes

Thuja occidentalis......................................................................dry and scaly eyelids